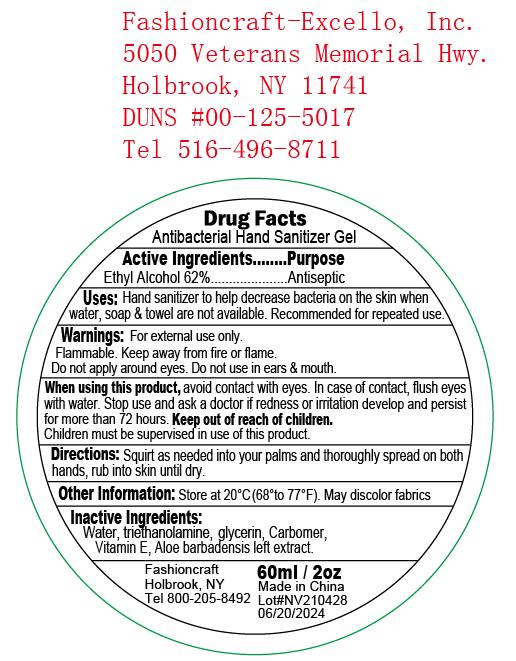 DRUG LABEL: Antibacterial Hand Sanitizer
NDC: 81131-001 | Form: GEL
Manufacturer: Hubei Flex Daily Chemicals CO., LTD
Category: otc | Type: HUMAN OTC DRUG LABEL
Date: 20220810

ACTIVE INGREDIENTS: ALCOHOL 62 mL/100 mL
INACTIVE INGREDIENTS: GLYCERIN; WATER; CARBOMER 940; TROLAMINE; ALOE VERA LEAF; .ALPHA.-TOCOPHEROL ACETATE

81131-001

Drug Fact

Active Ingredient(s)

Ethyl Alcohol 62%.

Purpose

Antiseptic

Use

Hand sanitizer to help decrease bacterial on the skkin when water, soap and towel are not available

Recommended for repeated use

Warnings

For external use only.

Flammable. Keep away from fire or flame

Do not apply around eyes. Do not use in ears and mouth.

When using this product, avoid contact with eyes. In case of contact, flush eyes with water

Stop use and ask a doctor if redness or irritation develop and persist for more than 72 hours.

Keep out of reach of children. Children must be spervised when use this product.

Directions

Squirt as needed into your palms and thoroughly spread on both hands, rub into skin until dry.

Other information

Store st 20C (68-77F)

May discolor some fabrics

Inactive ingredients

Water, glycerin, triethanolamine, carbomer, Vitamin E, aloe barbadensis leaf extract